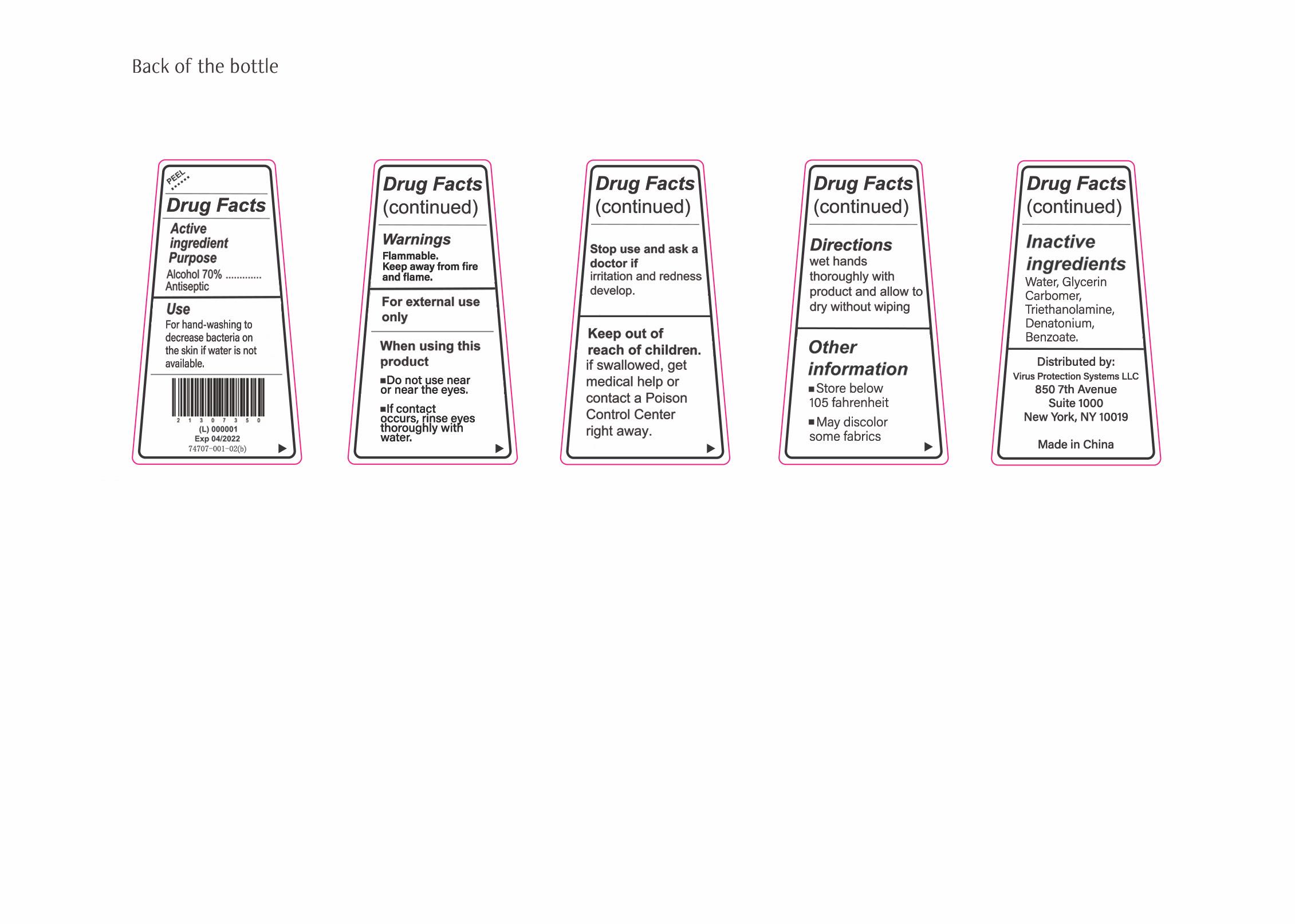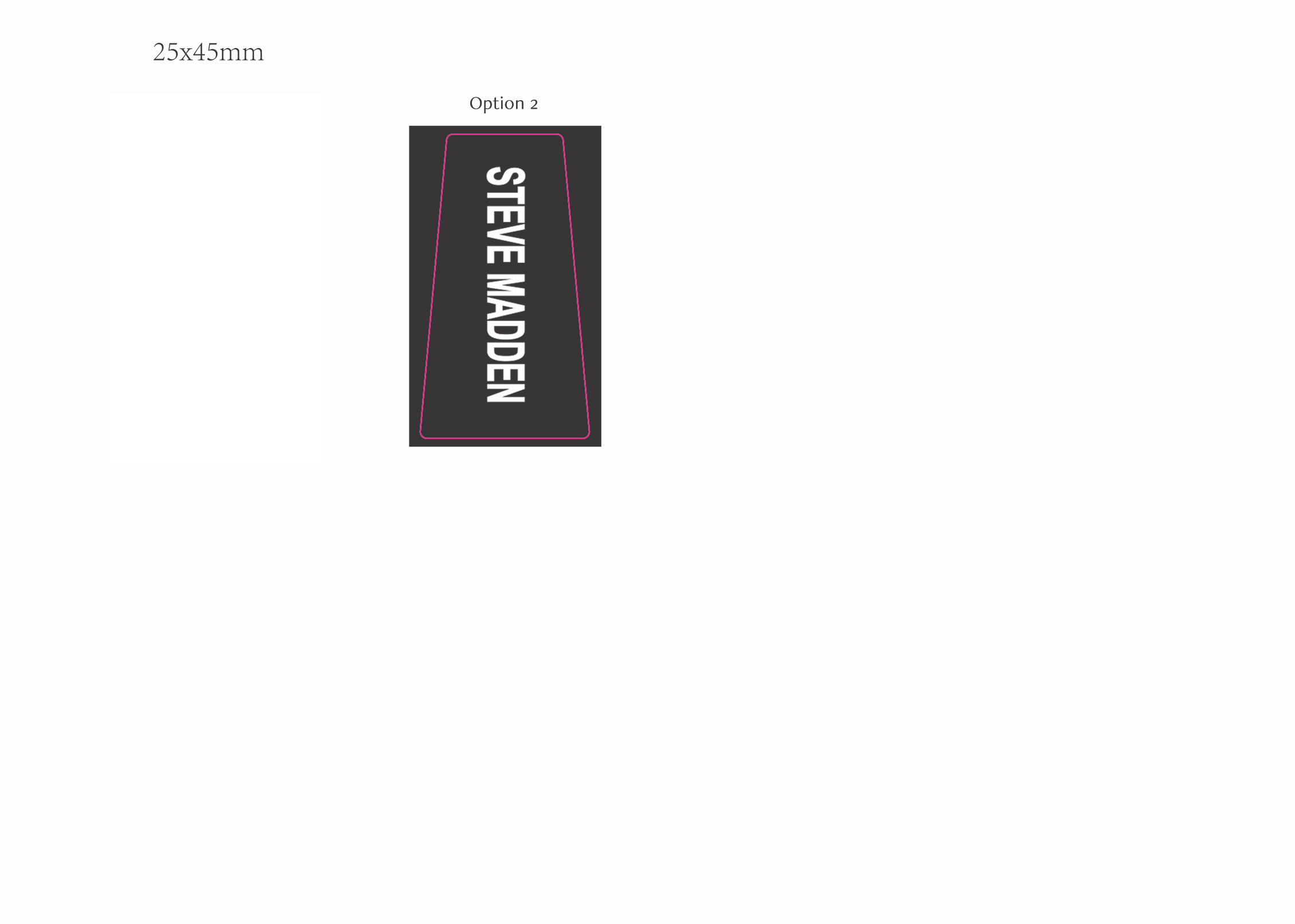 DRUG LABEL: Hand Sanitizer
NDC: 74707-001 | Form: LIQUID
Manufacturer: VIRUS PROTECTION SYSTEMS LLC
Category: otc | Type: HUMAN OTC DRUG LABEL
Date: 20200526

ACTIVE INGREDIENTS: ALCOHOL 70 mL/100 mL
INACTIVE INGREDIENTS: CARBOMER 1342 0.4 mL/100 mL; 2-((DIMETHYLAMINO)METHYL)-1,3-DIPHENYL-1-PROPANOL, ERYTHRO- 0.4 mL/100 mL; WATER 29.2 mL/100 mL

Steve Madden Hand Sanitizer "not for sale - for consumption only" - 30ML Marketing Samples

Active Ingredient(s)

Alcohol 70% Purpose: Antiseptic

Purpose

Antiseptic, Hand Sanitizer

Use

For hand-washing to decrease bacteria on the skin if water is not available.

Warnings

Flammable. Keep away from fire or flame

Do not use

Keep out of the reach of children

Do not use in or near the eyes

If contact occurs, rinse eyes thoroughly with water
stop use and ask a doctor irritation and redness develop

Stop use and ask a doctor if irritation and redness develop

Keep out of reach of children. If swallowed, get medical help or contact a Poison Control Center right away.

Directions

wet hands thoroughly with product and allow to dry without wiping

Other information

store below 105 fahrenheit

may discolor some fabrics

Inactive ingredients

water, glycerin, carbomer, triethanolamine, denatonium, benzoate

Package Label - Principal Display Panel

STEVE MADDEN